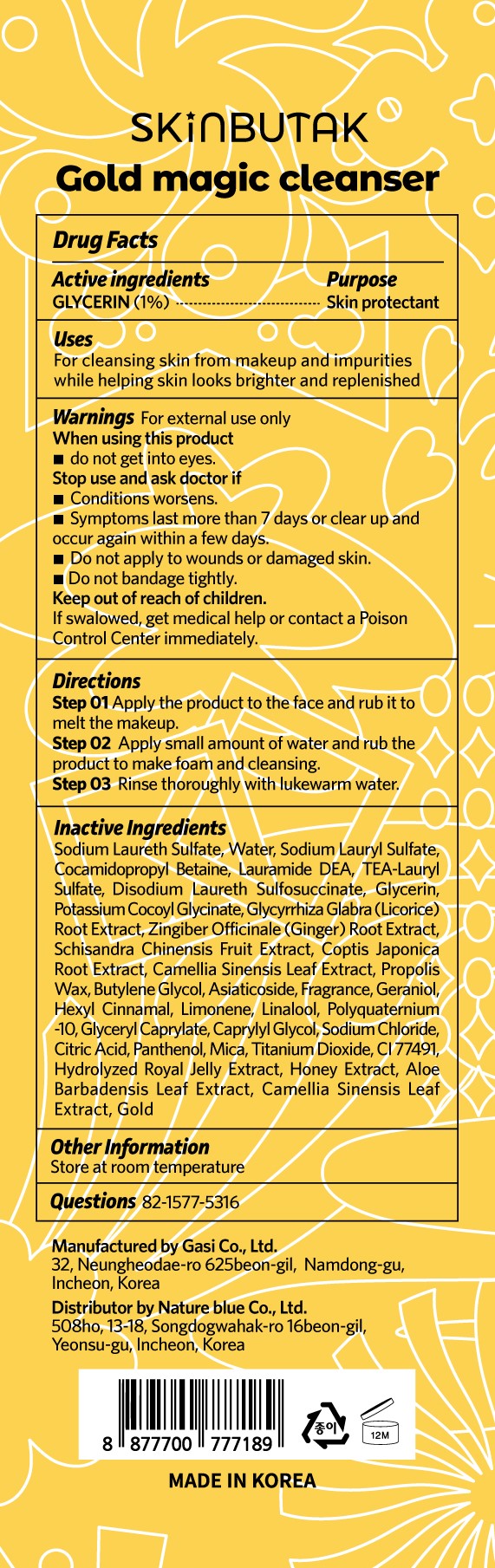 DRUG LABEL: SKINBUTAK GOLD MAGIC CLEANSER
NDC: 81851-204 | Form: GEL
Manufacturer: NatureBlue Co.,Ltd
Category: otc | Type: HUMAN OTC DRUG LABEL
Date: 20210429

ACTIVE INGREDIENTS: GLYCERIN 1 mg/100 mL
INACTIVE INGREDIENTS: GLYCERYL CAPRYLATE; DISODIUM LAURETH SULFOSUCCINATE; GINGER; COPTIS JAPONICA ROOT; PROPOLIS WAX; BUTYLENE GLYCOL; GERANIOL; GLYCYRRHIZA GLABRA; SCHISANDRA CHINENSIS FRUIT; .ALPHA.-HEXYLCINNAMALDEHYDE; SODIUM CHLORIDE; CITRIC ACID MONOHYDRATE; ALOE VERA LEAF; GOLD; SODIUM LAURETH-3 SULFATE; WATER; COCAMIDOPROPYL BETAINE; LAURIC DIETHANOLAMIDE; TRIETHANOLAMINE LAURYL SULFATE; POTASSIUM COCOYL GLYCINATE; ASIATICOSIDE; SODIUM LAURYL SULFATE; LINALOOL, (+/-)-; CAPRYLYL GLYCOL; MICA; HIPPOPHAE RHAMNOIDES FRUIT OIL; LIMONENE, (+)-; PANTHENOL; TITANIUM DIOXIDE; FERRIC OXIDE RED; HONEY; GREEN TEA LEAF; HIPPOPHAE RHAMNOIDES FRUIT

81851-204 SKINBUTAK GOLD MAGIC CLEANSER

Active ingredients

GLYCERIN (1%)

Purpose

Skin protectant

Uses

For cleansing skin from makeup and impurities while helping skin looks brighter and replenished

Warnings

For external use only.

If swalowed, get medical help or contact a Poison Control Center immediately.

When using this product

- do not get into eyes.

Stop use and ask doctor if

- Conditions worsens.
- Symptoms last more than 7 days or clear up and occur again within a few days.
- Do not apply to wounds or damaged skin.
- Do not bandage tightly.

Keep out of reach of children

Directions

Step 01 Apply the product to the face and rub it to melt the makeup.
Step 02 Apply small amount of water and rub the product to make foam and cleansing.
Step 03 Rinse thoroughly with lukewarm water.

Inactive Ingredients

Sodium Laureth Sulfate, Water, Sodium Lauryl Sulfate, Cocamidopropyl Betaine, Lauramide DEA, TEA-Lauryl Sulfate, Disodium Laureth Sulfosuccinate, Glycerin, Potassium Cocoyl Glycinate, Glycyrrhiza Glabra (Licorice) Root Extract, Zingiber Officinale (Ginger) Root Extract, Schisandra Chinensis Fruit Extract, Coptis Japonica Root Extract, Camellia Sinensis Leaf Extract, Propolis Wax, Butylene Glycol, Asiaticoside, Fragrance, Geraniol, Hexyl Cinnamal, Limonene, Linalool, Polyquaternium-10, Glyceryl Caprylate, Caprylyl Glycol, Sodium Chloride, Citric Acid, Panthenol, Mica, Titanium Dioxide, CI 77491, Hydrolyzed Royal Jelly Extract, Honey Extract, Aloe Barbadensis Leaf Extract, Camellia Sinensis Leaf Extract, Gold

Other Information

Store at room temperature